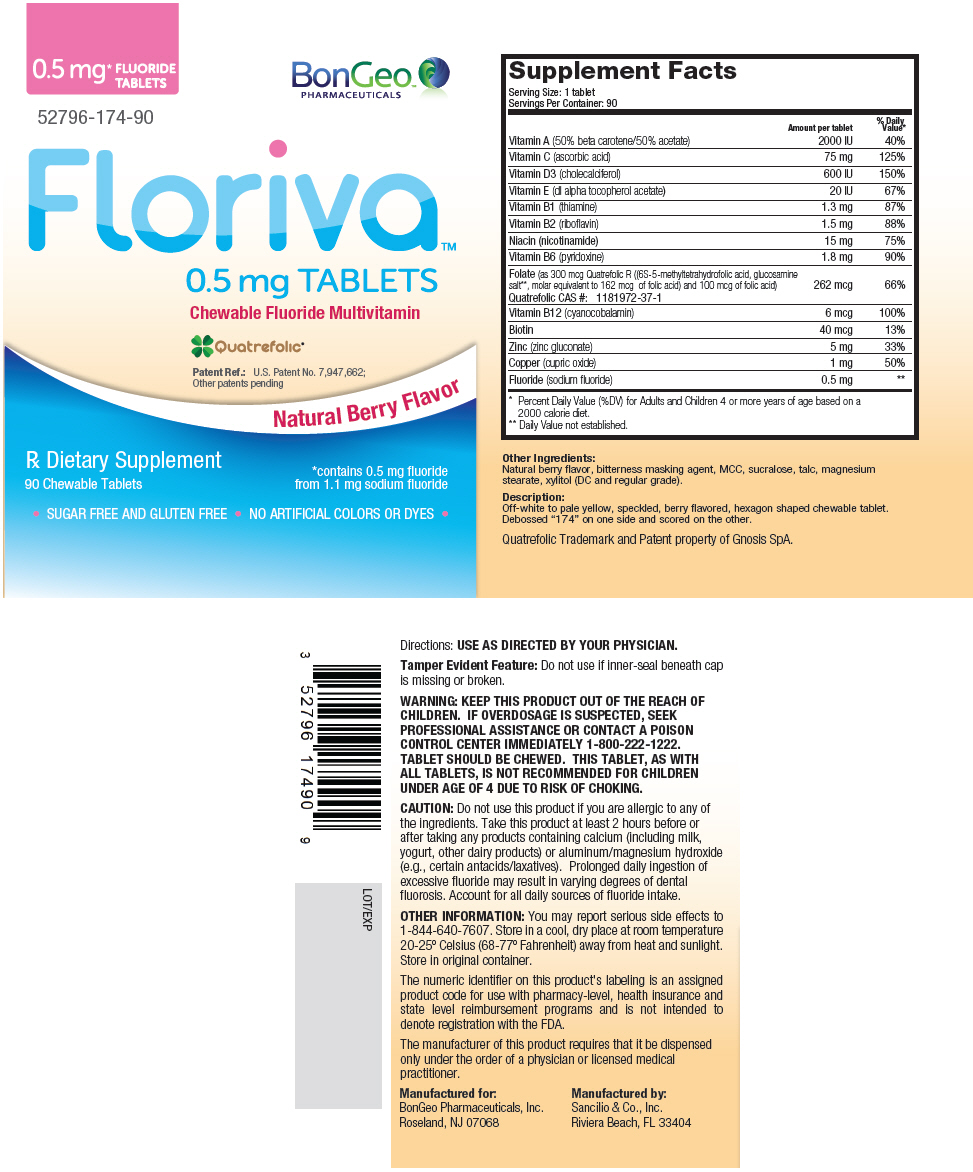 DRUG LABEL: Floriva
NDC: 52796-174 | Form: TABLET, CHEWABLE
Manufacturer: BonGeo Pharmaceuticals, Inc.
Category: prescription | Type: HUMAN PRESCRIPTION DRUG LABEL
Date: 20240202

ACTIVE INGREDIENTS: VITAMIN A ACETATE 1000 [iU]/1 1; BETA CAROTENE 1000 [iU]/1 1; Ascorbic acid 75 mg/1 1; CHOLECALCIFEROL 600 [iU]/1 1; .ALPHA.-TOCOPHEROL 20 [iU]/1 1; THIAMINE 1.3 mg/1 1; RIBOFLAVIN 1.5 mg/1 1; NIACINAMIDE 15 mg/1 1; PYRIDOXINE 1.8 mg/1 1; LEVOMEFOLATE GLUCOSAMINE 162 ug/1 1; FOLIC ACID 100 ug/1 1; CYANOCOBALAMIN 6 ug/1 1; BIOTIN 40 ug/1 1; ZINC GLUCONATE 5 mg/1 1; CUPRIC OXIDE 1 mg/1 1; SODIUM FLUORIDE 0.5 mg/1 1
INACTIVE INGREDIENTS: MICROCRYSTALLINE CELLULOSE; SUCRALOSE; TALC; MAGNESIUM STEARATE; XYLITOL

Floriva™
0.5 mg TABLETS

Supplement Facts
Serving Size: 1 tablet
Servings Per Container: 90
 | Amount per tablet | % Daily Value [Percent Daily Value (%DV) for Adults and Children 4 or more years of age based on a 2000 calorie diet.]
Vitamin A (50% beta carotene/50% acetate) | 2000 IU | 40%
Vitamin C (ascorbic acid) | 75 mg | 125%
Vitamin D3 (cholecalciferol) | 600 IU | 150%
Vitamin E (dl alpha tocopherol acetate) | 20 IU | 67%
Vitamin B1 (thiamine) | 1.3 mg | 87%
Vitamin B2 (riboflavin) | 1.5 mg | 88%
Niacin (nicotinamide) | 15 mg | 75%
Vitamin B6 (pyridoxine) | 1.8 mg | 90%
Folate (as 300 mcg Quatrefolic R ((6S-5-methyltetrahydrofolic acid, glucosamine salt [Daily Value not established.] , molar equivalent to 162 mcg of folic acid) and 100 mcg of folic acid) Quatrefolic CAS #: 1181972-37-1 | 262 mcg | 66%
Vitamin B12 (cyanocobalamin) | 6 mcg | 100%
Biotin | 40 mcg | 13%
Zinc (zinc gluconate) | 5 mg | 33%
Copper (cupric oxide) | 1 mg | 50%
Fluoride (sodium fluoride) | 0.5 mg

Other Ingredients

Natural berry flavor, bitterness masking agent, MCC, sucralose, talc, magnesium stearate, xylitol (DC and regular grade).

Description

Off-white to pale yellow, speckled, berry flavored, hexagon shaped chewable tablet. Debossed "174" on one side and scored on the other.

Directions

USE AS DIRECTED BY YOUR PHYSICIAN.

Tamper Evident Feature

Do not use if inner-seal beneath cap is missing or broken.

WARNING

KEEP THIS PRODUCT OUT OF THE REACH OF CHILDREN. IF OVERDOSAGE IS SUSPECTED, SEEK PROFESSIONAL ASSISTANCE OR CONTACT A POISON CONTROL CENTER IMMEDIATELY 1-800-222-1222. TABLET SHOULD BE CHEWED. THIS TABLET, AS WITH ALL TABLETS, IS NOT RECOMMENDED FOR CHILDREN UNDER AGE OF 4 DUE TO RISK OF CHOKING.

CAUTION

Do not use this product if you are allergic to any of the ingredients. Take this product at least 2 hours before or after taking any products containing calcium (including milk, yogurt, other dairy products) or aluminum/magnesium hydroxide (e.g., certain antacids/laxatives). Prolonged daily ingestion of excessive fluoride may result in varying degrees of dental fluorosis. Account for all daily sources of fluoride intake.

OTHER INFORMATION

You may report serious side effects to 1-844-640-7607. Store in a cool, dry place at room temperature 20-25º Celsius (68-77º Fahrenheit) away from heat and sunlight. Store in original container.

The numeric identifier on this product's labeling is an assigned product code for use with pharmacy-level, health insurance and state level reimbursement programs and is not intended to denote registration with the FDA.

The manufacturer of this product requires that it be dispensed only under the order of a physician or licensed medical practitioner.

Manufactured for:
BonGeo Pharmaceuticals, Inc.
Roseland, NJ 07068

Manufactured by:
Sancilio & Co., Inc.
Riviera Beach, FL 33404

LOT/EXP

Quatrefolic Trademark and Patent property of Gnosis SpA.

PRINCIPAL DISPLAY PANEL - 90 Tablet Bottle Label

0.5 mg*
FLUORIDE
TABLETS

BonGeo™
PHARMACEUTICALS

52796-174-90

Floriva™
0.5 mg TABLETS

Chewable Fluoride Multivitamin

Quatrefolic®

Patent Ref.: U.S. Patent No. 7,947,662;
Other patents pending

Natural Berry Flavor

Rx Dietary Supplement

90 Chewable Tablets

*contains 0.5 mg fluoride
from 1.1 mg sodium fluoride

• SUGAR FREE AND GLUTEN FREE • NO ARTIFICIAL COLORS OR DYES •